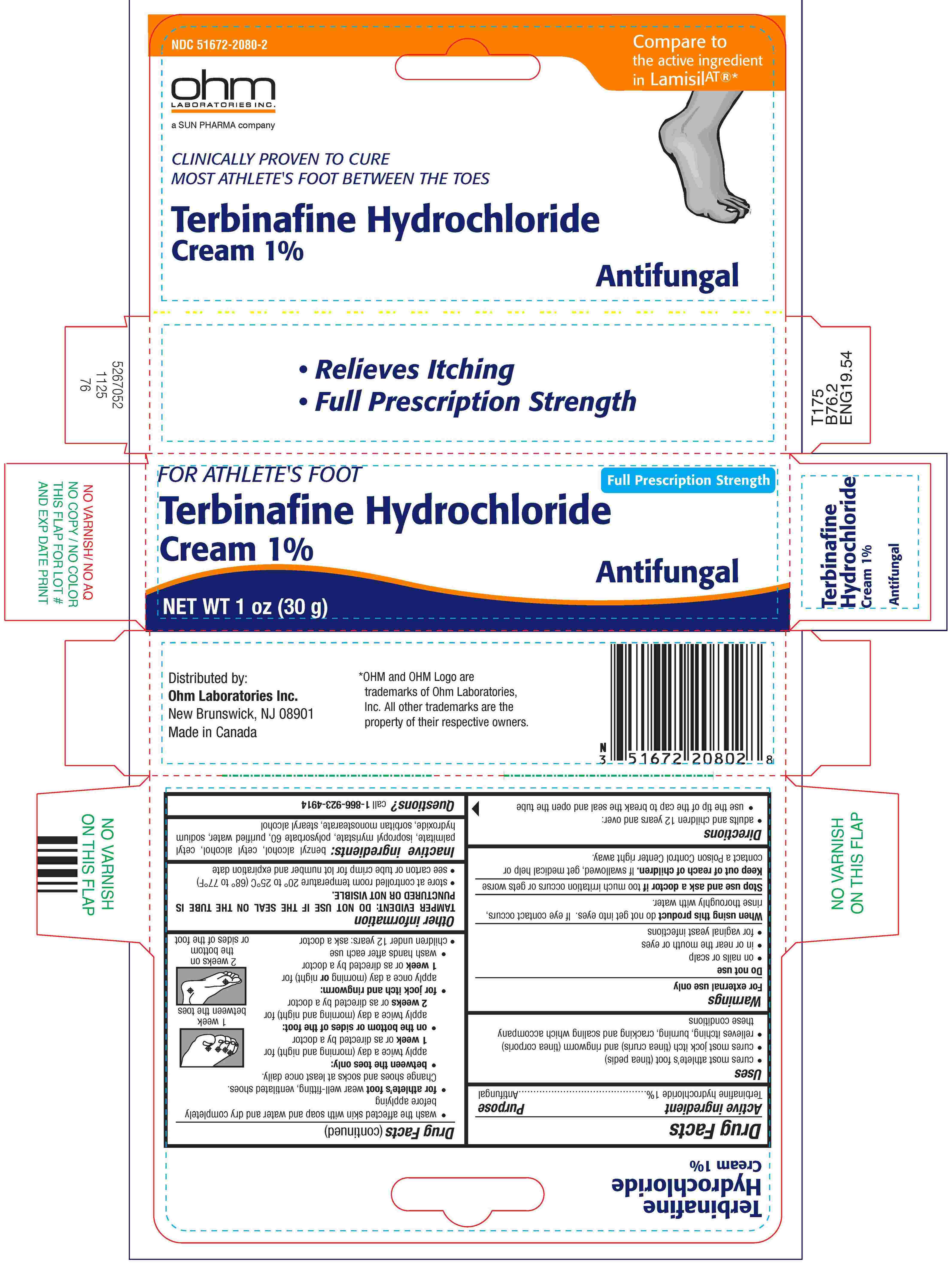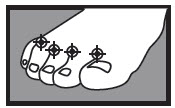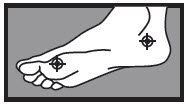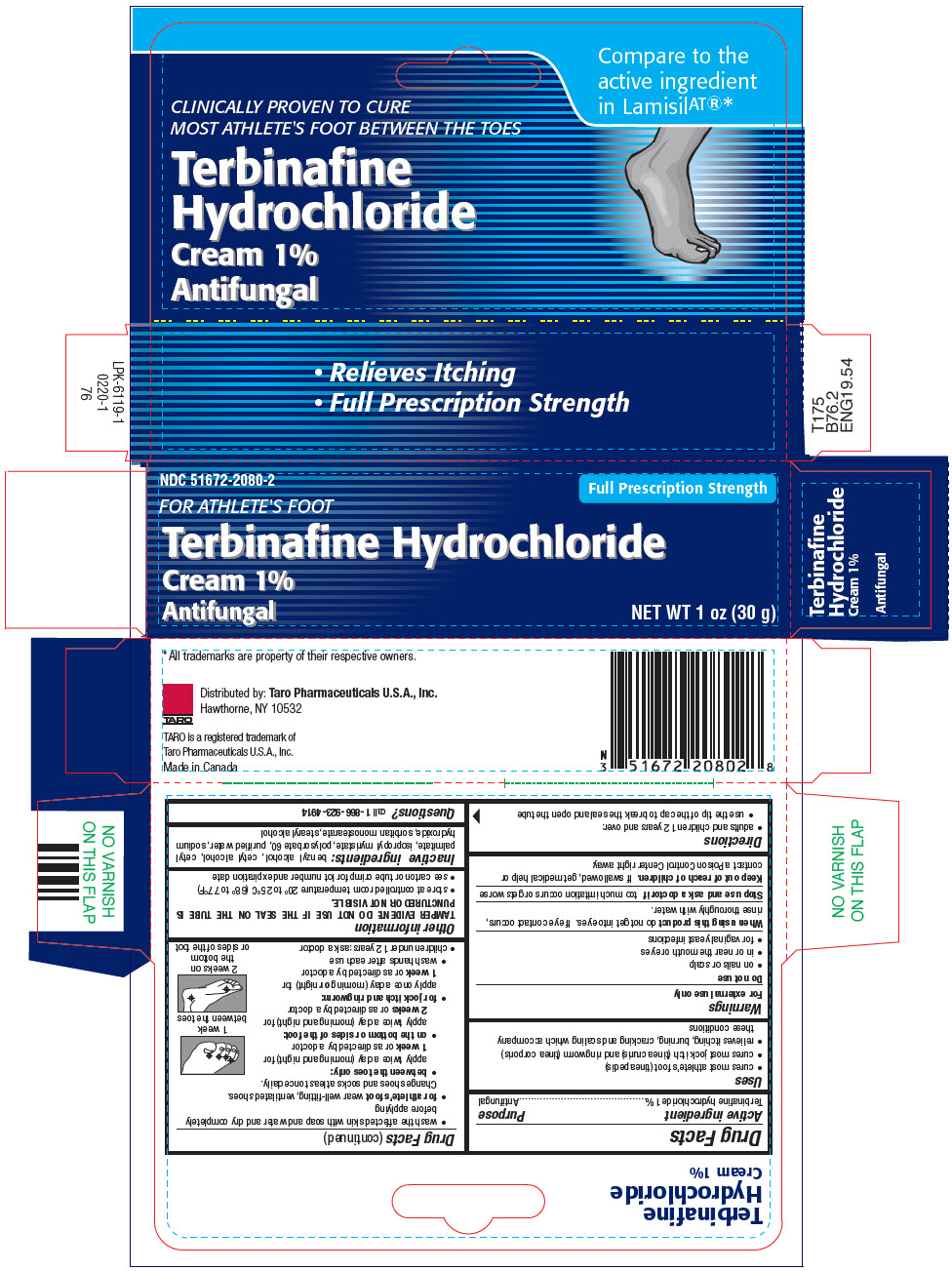 DRUG LABEL: Terbinafine Hydrochloride
NDC: 51672-2080 | Form: CREAM
Manufacturer: Sun Pharmaceutical Industries, Inc.
Category: otc | Type: HUMAN OTC DRUG LABEL
Date: 20260220

ACTIVE INGREDIENTS: TERBINAFINE HYDROCHLORIDE 1 g/100 g
INACTIVE INGREDIENTS: BENZYL ALCOHOL; CETYL ALCOHOL; CETYL PALMITATE; ISOPROPYL MYRISTATE; POLYSORBATE 60; WATER; SODIUM HYDROXIDE; SORBITAN MONOSTEARATE; STEARYL ALCOHOL

Terbinafine Hydrochloride
Cream 1%
Antifungal Cream

Drug Facts

Active ingredient

Terbinafine hydrochloride 1%

Purpose

Antifungal

Uses

- cures most athlete's foot (tinea pedis)
- cures most jock itch (tinea cruris) and ringworm (tinea corporis)
- relieves itching, burning, cracking and scaling which accompany these conditions

Warnings

For external use only

Do not use

- on nails or scalp
- in or near the mouth or eyes
- for vaginal yeast infections

WHEN USING

When using this productdo not get into eyes. If eye contact occurs, rinse thoroughly with water.

Stop use and ask a doctor iftoo much irritation occurs or gets worse

Keep out of reach of children.If swallowed, get medical help or contact a Poison Control Center right away.

Directions

- adults and children 12 years and over: - use the tip of the cap to break the seal and open the tube - wash the affected skin with soap and water and dry completely before applying - for athlete's footwear well-fitting, ventilated shoes. Change shoes and socks at least once daily. - between the toes only: apply twice a day (morning and night) for 1 weekor as directed by a doctor - on the bottom or sides of the foot: apply twice a day (morning and night) for 2 weeksor as directed by a doctor - for jock itch and ringworm: apply once a day (morning ornight) for 1 weekor as directed by a doctor - wash hands after each use - children under 12 years: ask a doctor | 1 week between the toes 2 weeks on the bottom or sides of the foot

Other information

TAMPER EVIDENT: DO NOT USE IF THE SEAL ON THE TUBE IS PUNCTURED OR NOT VISIBLE.

- store at controlled room temperature 20° to 25°C (68° to 77°F)
- see carton or tube crimp for lot number and expiration date

Inactive ingredients

benzyl alcohol, cetyl alcohol, cetyl palmitate, isopropyl myristate, polysorbate 60, purified water, sodium hydroxide, sorbitan monostearate, stearyl alcohol

Questions?

call 1-866-923-4914

Distributed by:

Ohm Loaboratories Inc.

New Brunswick, NJ 08901

Made in Canada

PRINCIPAL DISPLAY PANEL - 30 g Tube Carton

NDC 51672-2080-2
Full Prescription Strength

FOR ATHLETE'S FOOT

Terbinafine Hydrochloride
Cream 1%
Antifungal

NET WT 1 oz (30 g)